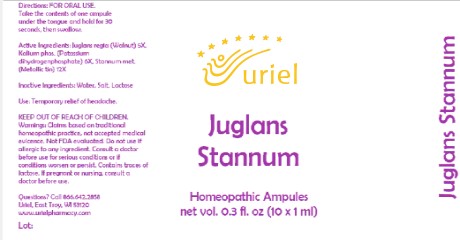 DRUG LABEL: Juglans Stannum
NDC: 48951-6078 | Form: LIQUID
Manufacturer: Uriel Pharmacy Inc.
Category: homeopathic | Type: HUMAN OTC DRUG LABEL
Date: 20210528

ACTIVE INGREDIENTS: JUGLANS REGIA LEAF 5 [hp_X]/1 mL; POTASSIUM PHOSPHATE, MONOBASIC 6 [hp_X]/1 mL; TIN 12 [hp_X]/1 mL
INACTIVE INGREDIENTS: WATER; SODIUM CHLORIDE; LACTOSE

Juglans Stannum

INDICATIONS AND USAGE

Directions: FOR ORAL USE.

DOSAGE AND ADMINISTRATION

Take the contents of one ampule under the tongue and hold for 30 seconds, then swallow.

ACTIVE INGREDIENT

Active Ingredients: Juglans regia e fol. et fruct. 5X, Kalium phosphoricum 6X, Stannum metallicum 12X

Inactive Ingredients: Water, Salt, Lactose

PURPOSE

Use: Temporary relief of headache.

KEEP OUT OF REACH OF CHILDREN.

WARNINGS

Warnings: Claims based on traditional homeopathic practice, not accepted medical evicence. Not FDA evaluated. Do not use if allergic to any ingredient. Consult a doctor before use for serious conditions or if conditions worsen or persist. Contains traces of lactose. If pregnant or nursing, consult a doctor before use.

Questions? Call 866.642.2858

Uriel, East Troy, WI 53120

www.urielpharmacy.com